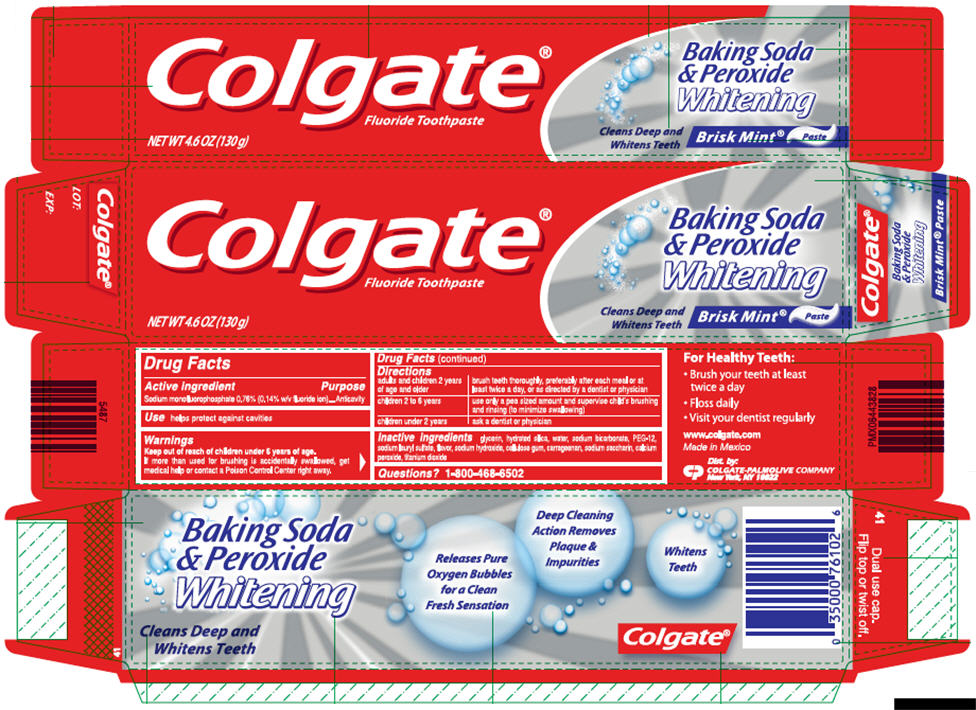 DRUG LABEL: COLGATE
NDC: 35000-959 | Form: PASTE, DENTIFRICE
Manufacturer: COLGATE PALMOLIVE COMPANY
Category: otc | Type: HUMAN OTC DRUG LABEL
Date: 20231229

ACTIVE INGREDIENTS: SODIUM MONOFLUOROPHOSPHATE 1 mg/1 g
INACTIVE INGREDIENTS: GLYCERIN 491.6 mg/1 g; HYDRATED SILICA; WATER; SODIUM BICARBONATE; POLYETHYLENE GLYCOL 600; SODIUM LAURYL SULFATE; SODIUM HYDROXIDE; CARBOXYMETHYLCELLULOSE SODIUM, UNSPECIFIED; CARRAGEENAN; SACCHARIN SODIUM; CALCIUM PEROXIDE; TITANIUM DIOXIDE

Colgate® Baking Soda and Peroxide Whitening Brisk Mint® Large Size Fluoride Toothpaste

Drug Facts

Active ingredient

Sodium monofluorophosphate 0.76% (0.14% w/v fluoride ion)

Purpose

Anticavity

Use

helps protect against cavities

Warnings

Keep out of reach of children under 6 years of age.

ASK DOCTOR

If more than used for brushing is accidentally swallowed, get medical help or contact a Poison Control Center right away.

Directions

adults and children 2 years of age and older | brush teeth thoroughly, preferably after each meal or at least twice a day, or as directed by a dentist or physician
children 2 to 6 years | use only a pea sized amount and supervise child's brushing and rinsing (to minimize swallowing)
children under 2 years | ask a dentist or physician

Inactive ingredients

glycerin, hydrated silica, water, sodium bicarbonate, PEG-12, sodium lauryl sulfate, flavor, sodium hydroxide, cellulose gum, carrageenan, sodium saccharin, calcium peroxide, titanium dioxide

Questions?

1-800-468-6502

Dist. by:
COLGATE-PALMOLIVE COMPANY
New York, NY 10022

PRINCIPAL DISPLAY PANEL - 130 g Carton

Colgate®
Fluoride Toothpaste

NET WT 4.6 OZ (130 g)

Baking Soda
& Peroxide
Whitening

Cleans Deep and
Whitens Teeth

Brisk Mint® Paste